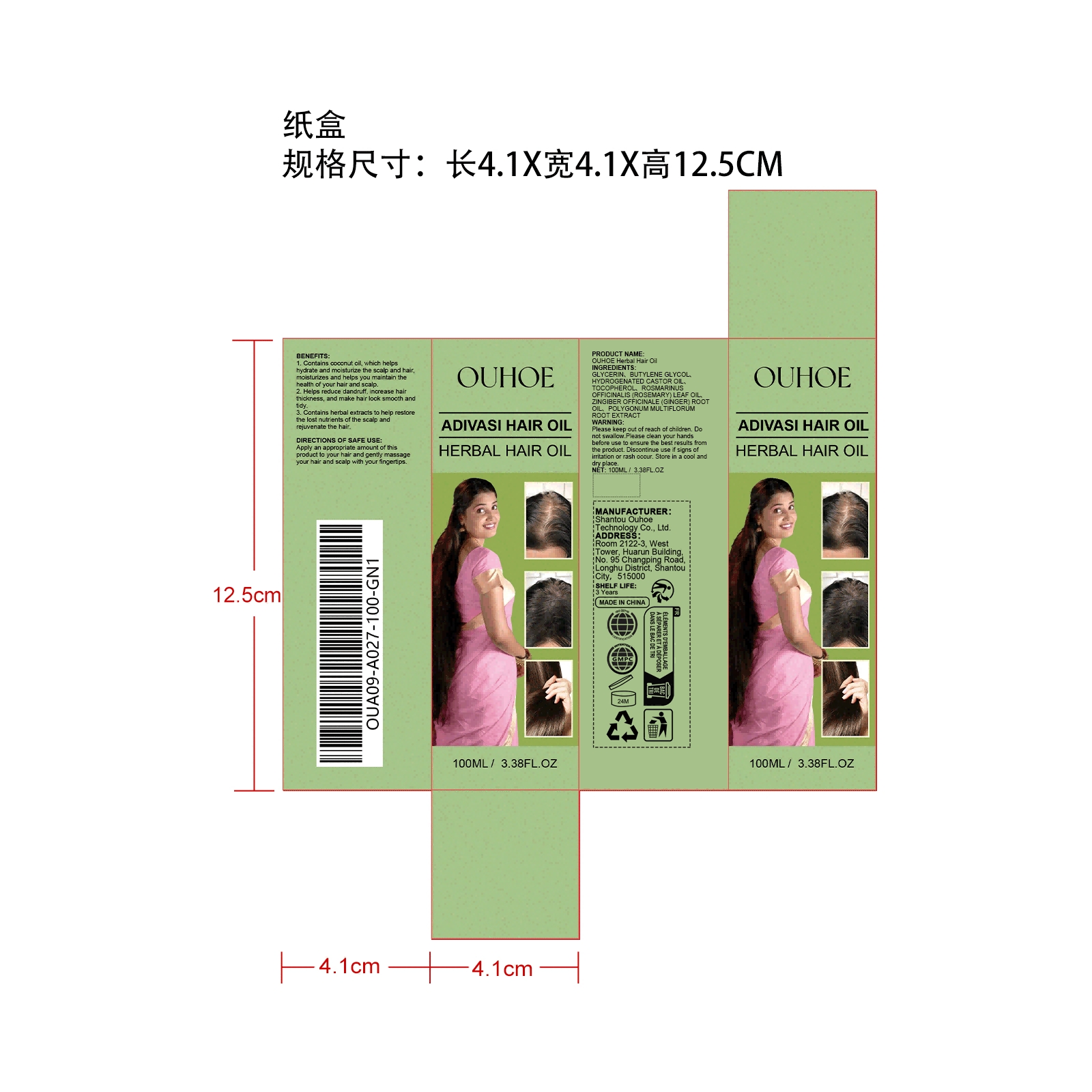 DRUG LABEL: OUHOE Herbal Hair Oil
NDC: 85163-002 | Form: LIQUID
Manufacturer: Shantou Ouhoe Technology Co., Ltd.
Category: otc | Type: HUMAN OTC DRUG LABEL
Date: 20251127

ACTIVE INGREDIENTS: REYNOUTRIA MULTIFLORA ROOT 0.02 mg/100 mg; ROSMARINUS OFFICINALIS (ROSEMARY) LEAF OIL 0.02 mg/100 mg; ZINGIBER OFFICINALE (GINGER) ROOT OIL 0.02 mg/100 mg
INACTIVE INGREDIENTS: BUTYLENE GLYCOL 40 mg/100 mg; TOCOPHEROL 0.02 mg/100 mg; HYDROGENATED CASTOR OIL 0.5 mg/100 mg; GLYCERIN 59.42 mg/100 mg

ACTIVE INGREDIENT

ROSMARINUS OFFICINALIS (ROSEMARY) LEAF OIL
ZINGIBER OFFICINALE (GINGER) ROOT OIL
REYNOUTRIA MULTIFLORA ROOT

PURPOSE

1. Contains coconut oll, which helps hydrate and moisturize the scalp and hairmoisturizes and helps you maintain thehealth of your hair and scalp.

2. Helps reduce dandruff,increase hair thickness, and make hair lock smooth and tiay.

3. Conlains herbal extracls to help restore the lost nulrients of the scalp and rejuvenate the hair.

WHEN USING

Apply appropriate amount of this product to hair and gently massage with fingertips.

STOP USE

Discontinue use if sians of irritation or rash occur.

DO NOT USE

Discontinue use if sians of irritation or rash occur.

KEEP OUT OF REACH OF CHILDREN

Please keep out of reach of children. Do not swallow.

WARNINGS

Please keep out of reach of children. Do not swallow.Please clean your hands before use to ensure the best results from the product.Discontinue use if sians of irritation or rash occur. Store in a cool and dry.

STORAGE AND HANDLING

Store in a cool and dry.

INACTIVE INGREDIENT

GLYCERIN
BUTYLENE GLYCOL
HYDROGENATED CASTOR OIL
TOCOPHEROL